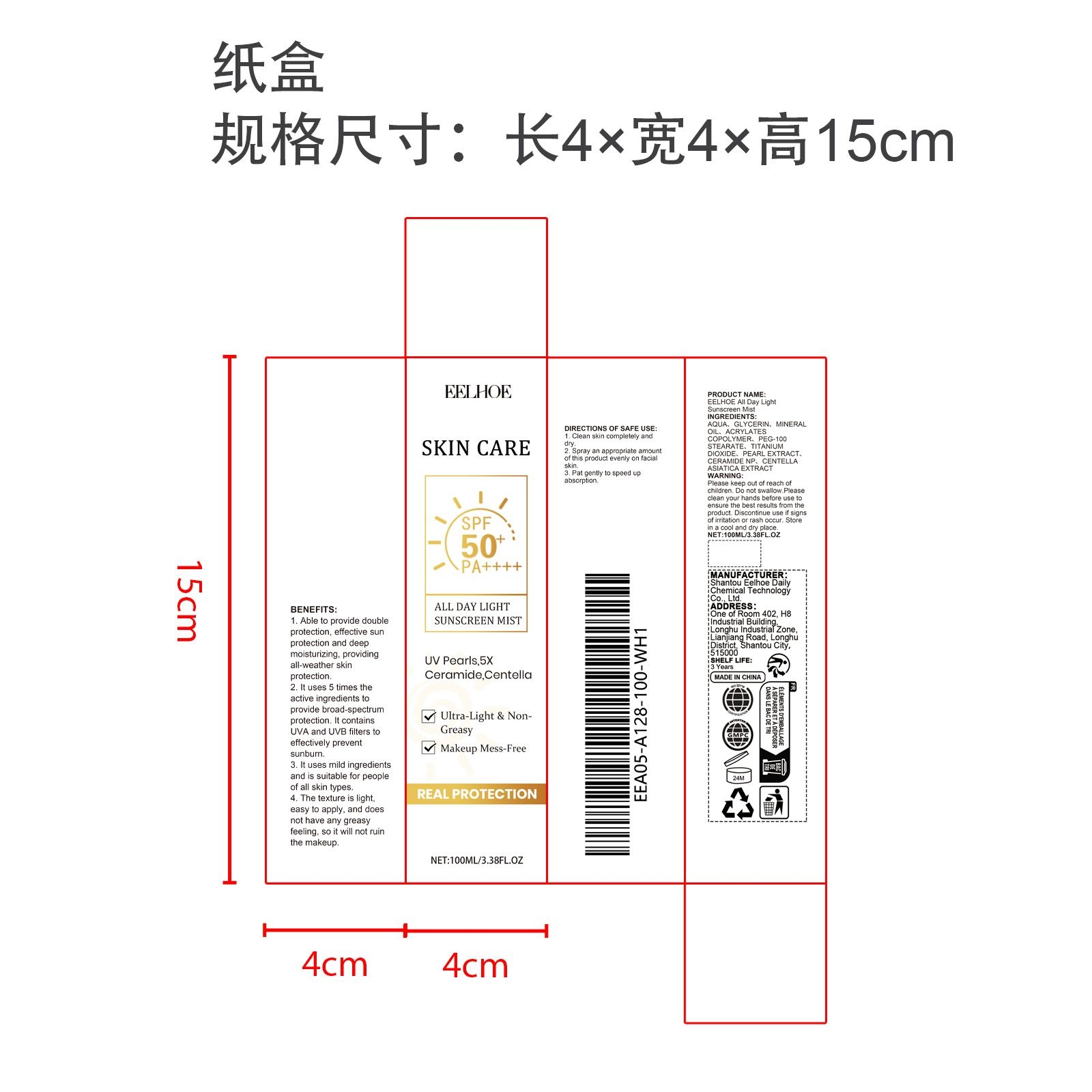 DRUG LABEL: EELHOE All Day Light Sunscreen Mist
NDC: 85064-022 | Form: LIQUID
Manufacturer: Shantou Eelhoe Daily Chemical Technology Co., Ltd.
Category: otc | Type: HUMAN OTC DRUG LABEL
Date: 20251205

ACTIVE INGREDIENTS: PEARL (HYRIOPSIS CUMINGII) 0.02 mg/100 mg; CENTELLA ASIATICA 0.02 mg/100 mg
INACTIVE INGREDIENTS: TITANIUM DIOXIDE 1 mg/100 mg; MINERAL OIL 3 mg/100 mg; GLYCERIN 3 mg/100 mg; CERAMIDE NP 0.02 mg/100 mg; SODIUM ACRYLATES CROSSPOLYMER-2 2 mg/100 mg; AQUA 88.94 mg/100 mg; PEG-100 STEARATE 2 mg/100 mg

ACTIVE INGREDIENT

PEARL EXTRACT、CENTELLA ASIATICA EXTRACT

PURPOSE

1. Able to provide double protection, effective sun protection and deep moisturizing, providing all-weather skin protection

2. It uses 5 times the active ingredients to provide broad-spectrum protection. It contains UVA and UVB filters to effectively prevent sunburn.

3. It uses mild ingredients and is suitable for people of all skin types.

4. The texture is light, easy to apply, and does not have any greasy feeling, so it will not ruin the makeup.

WHEN USING

1. Clean skin completely and dry

2. Spray an appropriate amount of this product evenly on facial skin

3. Pat gently to speed up absorption.

WARNINGS

Please keep out of reach of children. Do not swallow.Please clean your hands before use to ensure the best results from the product. Discontinue use if signs of irritation or rash occur. Store in a cool and dry place.

DO NOT USE

Discontinue use if signs of irritation or rash occur.

STOP USE

Discontinue use if signs of irritation or rash occur.

KEEP OUT OF REACH OF CHILDREN

Please keep out of reach of children. Do not swallow.

STORAGE AND HANDLING

Store in a cool and dry place.

INACTIVE INGREDIENT

AQUA、GLYCERIN、MINERAL OIL、ACRYLATES COPOLYMER、PEG-100 STEARATE、TITANIUM DIOXIDE、CERAMIDE NP

INDICATIONS AND USAGE

1. Clean skin completely and dry

2. Spray an appropriate amount of this product evenly on facial skin

3. Pat gently to speed up absorption.

DOSAGE AND ADMINISTRATION

1. Clean skin completely and dry

2. Spray an appropriate amount of this product evenly on facial skin

3. Pat gently to speed up absorption.